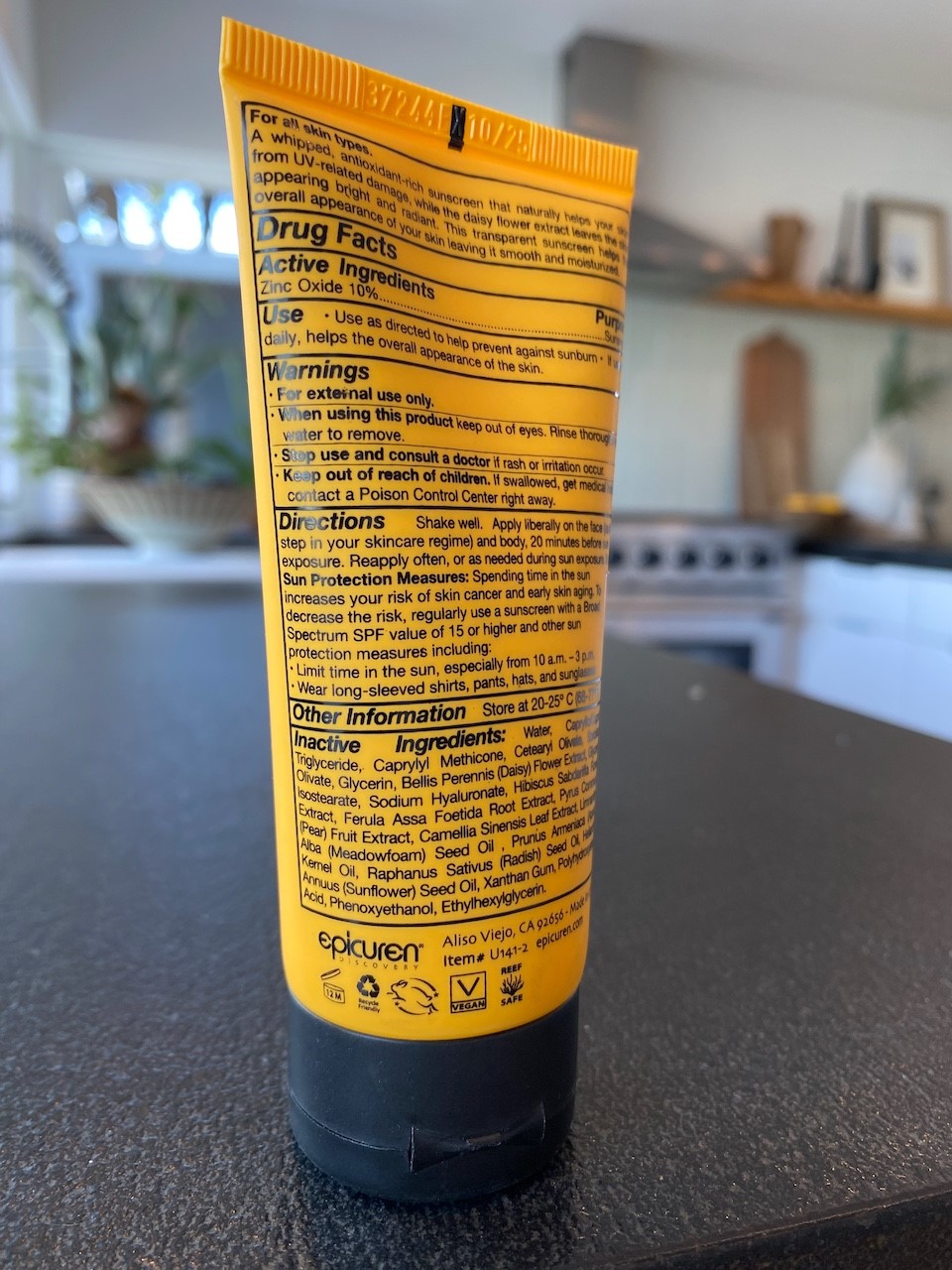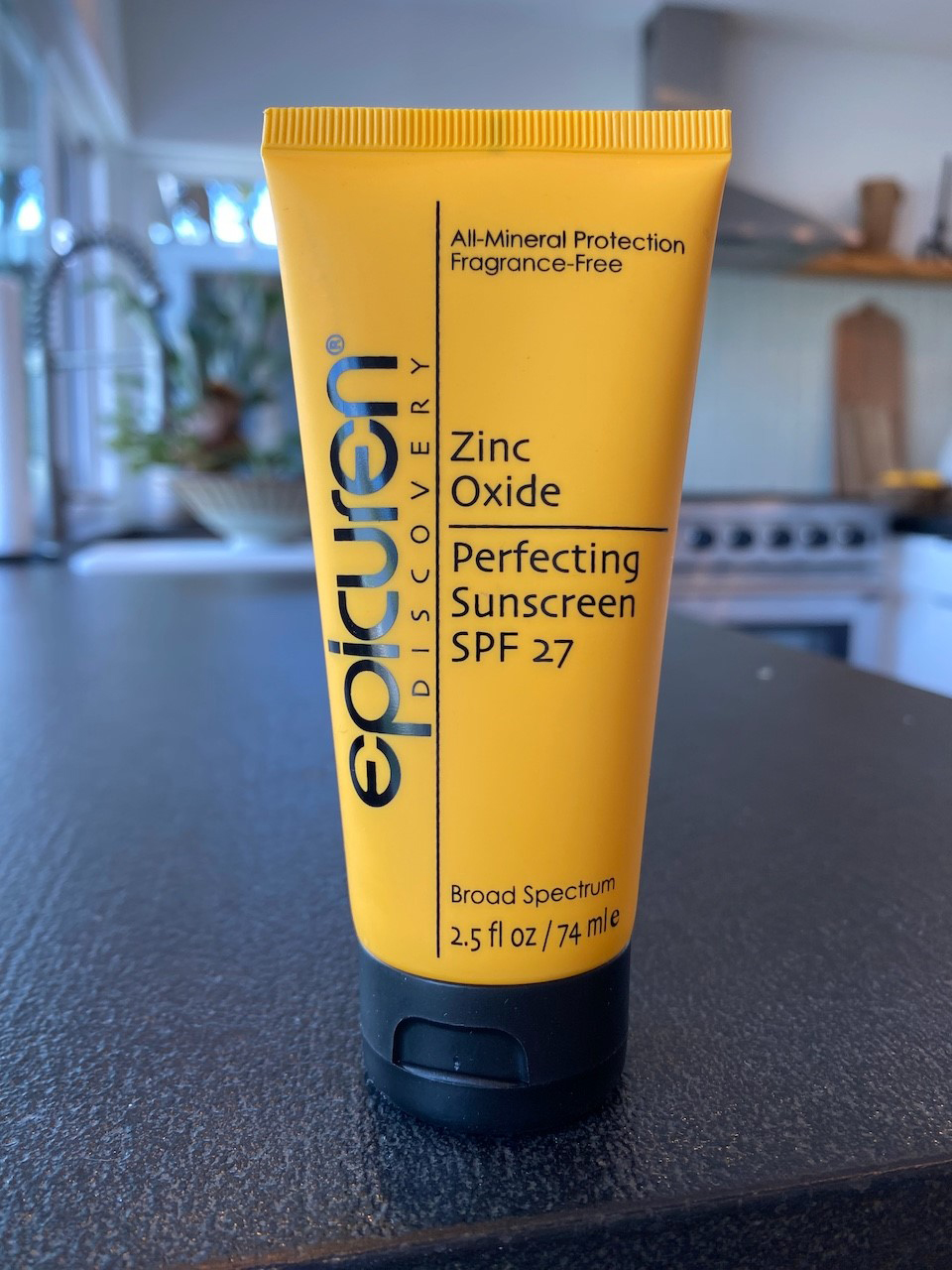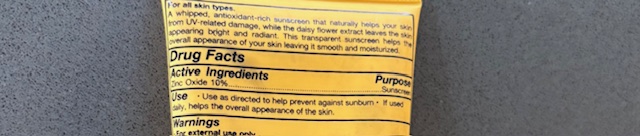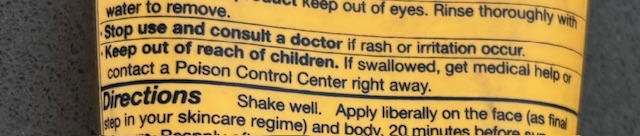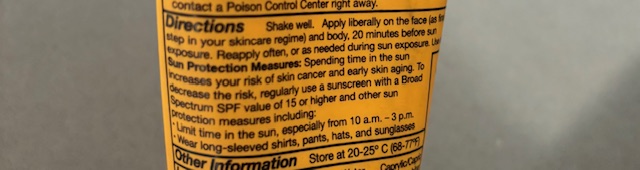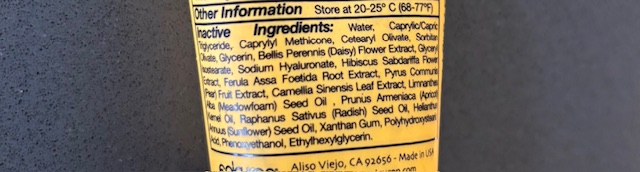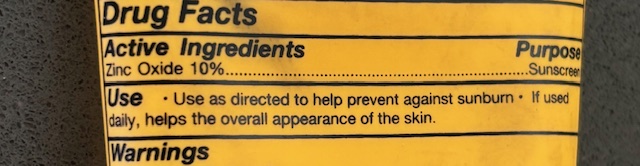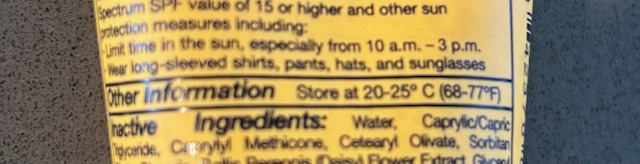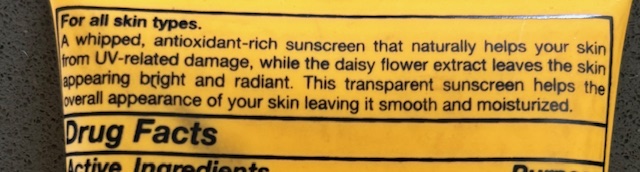 DRUG LABEL: Zinc Oxide Perfecting Sunscreen
NDC: 84378-100 | Form: CREAM
Manufacturer: Epicuren Discovery
Category: otc | Type: HUMAN OTC DRUG LABEL
Date: 20250729

ACTIVE INGREDIENTS: ZINC OXIDE 10 g/100 g
INACTIVE INGREDIENTS: PEAR; SORBITAN OLIVATE; MEDIUM-CHAIN TRIGLYCERIDES; POLYHYDROXYSTEARIC ACID (2300 MW); WATER; CAPRYLYL TRISILOXANE; CETEARYL OLIVATE; GLYCERIN; BELLIS PERENNIS FLOWER; GLYCERYL ISOSTEARATE; HYALURONATE SODIUM; HIBISCUS SABDARIFFA FLOWER; FERULA ASSA-FOETIDA ROOT; GREEN TEA LEAF; MEADOWFOAM SEED OIL; APRICOT KERNEL OIL; RAPHANUS SATIVUS VAR. SATIVUS SEED; XANTHAN GUM; PHENOXYETHANOL; ETHYLHEXYLGLYCERIN

Zinc Oxide Perfecting Sunscreen SPF 27